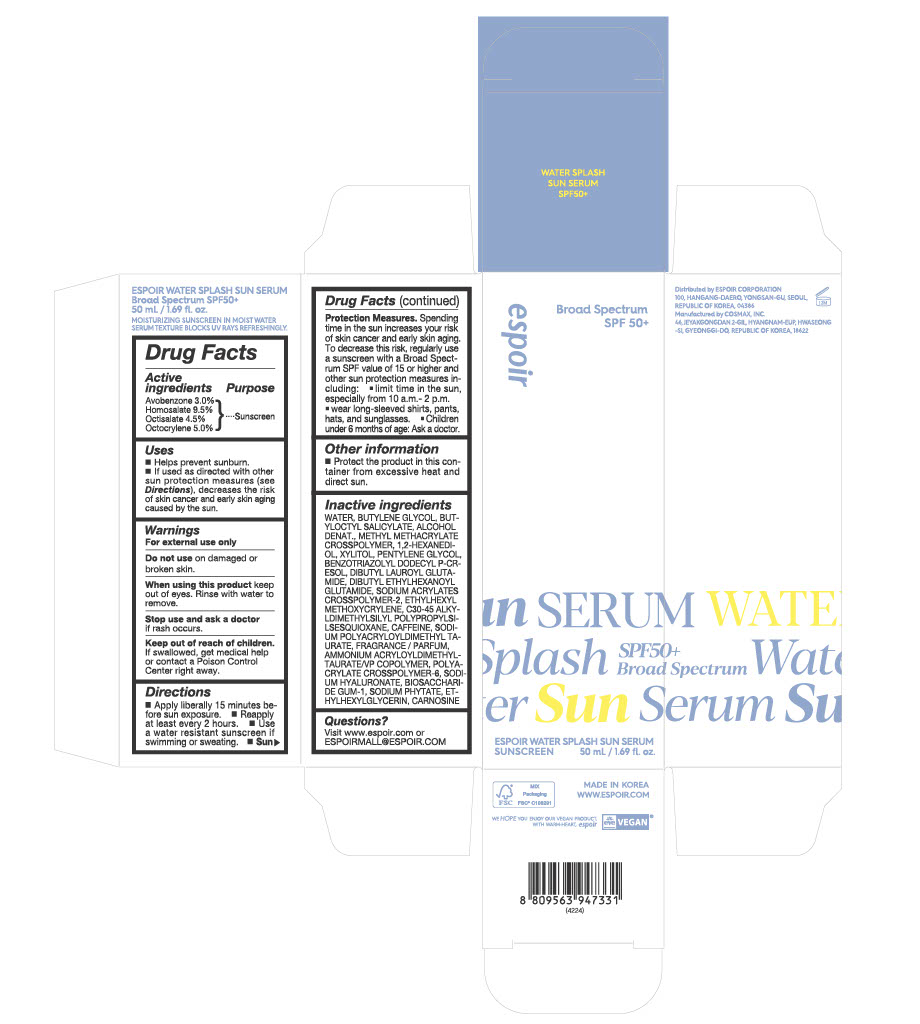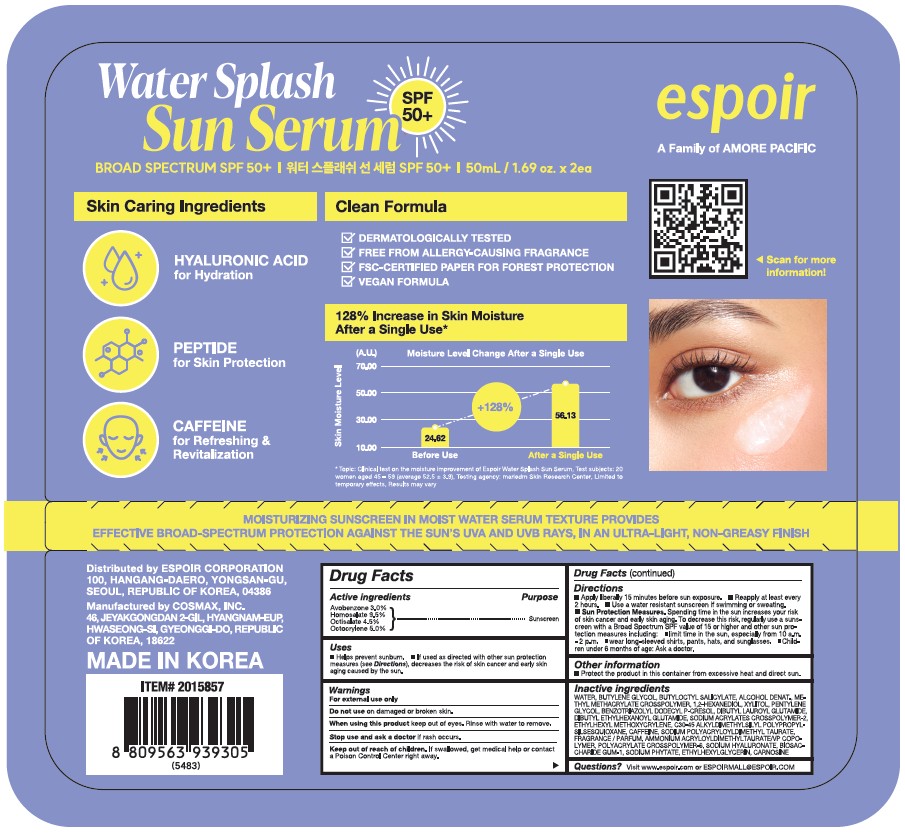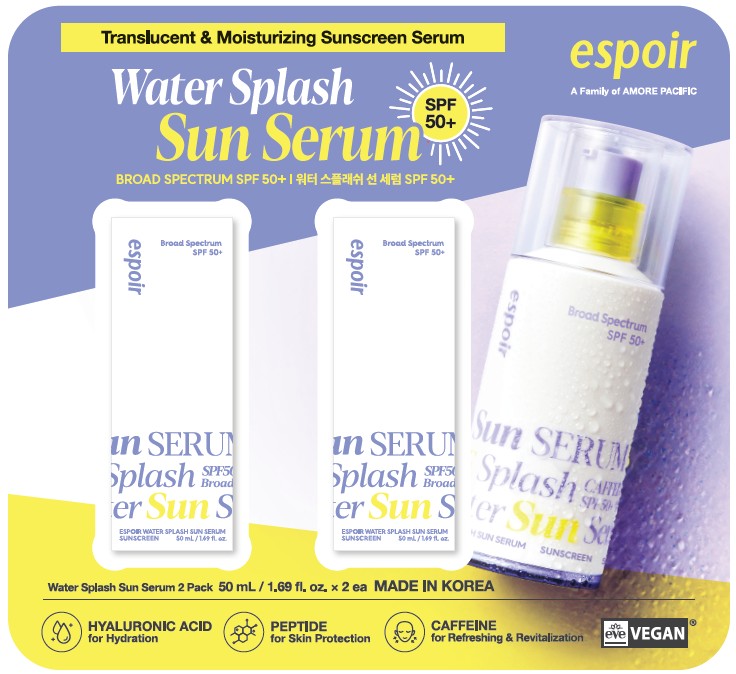 DRUG LABEL: ESPOIR WATER SPLASH SUN SERUM
NDC: 84469-721 | Form: LOTION
Manufacturer: ESPOIR Corporation
Category: otc | Type: HUMAN OTC DRUG LABEL
Date: 20250923

ACTIVE INGREDIENTS: AVOBENZONE 30 mg/1 mL; HOMOSALATE 95 mg/1 mL; OCTISALATE 45 mg/1 mL; OCTOCRYLENE 50 mg/1 mL
INACTIVE INGREDIENTS: SODIUM PHYTATE; BIOSACCHARIDE GUM-1; ALCOHOL 95%; METHYL METHACRYLATE/GLYCOL DIMETHACRYLATE CROSSPOLYMER; SODIUM ACRYLATES CROSSPOLYMER-2; 1,2-HEXANEDIOL; PENTYLENE GLYCOL; XYLITOL; BENZOTRIAZOLYL DODECYL P-CRESOL; CARNOSINE; BUTYLENE GLYCOL; WATER; BUTYLOCTYL SALICYLATE; CAFFEINE; POLYACRYLATE CROSSPOLYMER-6; ETHYLHEXYLGLYCERIN; DIBUTYL ETHYLHEXANOYL GLUTAMIDE; ETHYLHEXYL METHOXYCRYLENE; AMMONIUM ACRYLOYLDIMETHYLTAURATE/VP COPOLYMER; SODIUM POLYACRYLOYLDIMETHYL TAURATE; SODIUM HYALURONATE; DIBUTYL LAUROYL GLUTAMIDE

ESPOIR WATER SPLASH SUN SERUM Broad Spectrum SPF 50+

Drug Facts

Active ingredients

Avobenzone 3.0%

Homosalate 9.5%

Octisalate 4.5%

Octocrylene 5.0%

Purpose

Sunscreen

Uses

■ Helps prevent sunburn.

■ If used as directed with other sun protection measures (see Directions), decreases the risk of skin cancer and early skin aging caused by the sun.

Warnings

For external use only

Do not use

on damaged or broken skin.

When using this product

keep out of eyes. Rinse with water to remove.

Stop use and ask a doctor if

rash occurs.

Keep out of reach of children.

If swallowed, get medical help or contact a Poison Control Center right away.

Directions

■ Apply liberally 15 minutes before sun exposure.

■ Reapply at least every 2 hours.

■ Use a water resistant sunscreen if swimming or sweating.

■ Sun Protection Measures. Spending time in the sun increases your risk of skin cancer and early skin aging. To decrease this risk, regularly use a sunscreen with a Broad Spectrum SPF value of 15 or higher and other sun protection measures including:

■ limit time in the sun, especially from 10 a.m.- 2 p.m.

■ wear long-sleeved shirts, pants, hats, and sunglasses.

■ Children under 6 months of age: Ask a doctor.

Other information

■ Protect the product in this container from excessive heat and direct sun.

Inactive ingredients

WATER, BUTYLENE GLYCOL, BUTYLOCTYL SALICYLATE, ALCOHOL DENAT, METHYL METHACRYLATE CROSSPOLYMER, 12-HEXANEDIOL, XYLITOL, PENTYLENE GLYCOL, BENZOTRIAZOLYL DODECYL P-CRESOL, DIBUTYL LAUROYL GLUTAMIDE, DIBUTYL ETHYLHEXANOYL GLUTAMIDE, SODIUM ACRYLATES CROSSPOLYMER-2, ETHYLHEXYL METHOXYCRYLENE, C30-45 ALKYLDIMETHYLSILYL POLYPROPYLSILSESQUIOXANE, CAFFEINE, SODIUM POLYACRYLOYLDIMETHYLTAURATE, FRAGRANCE / PARFUM, AMMONIUM ACRYLOYLDIMETHYLTAURATE/VP COPOLYMER, POLYACRYLATE CROSSPOLYMER-6, SODIUM HYALURONATE, BIOSACCHARIDE GUM-1, SODIUM PHYTATE, ETHYLHEXYLGLYCERIN, CARNOSINE

Questions?

Visit www.espoir.com or
ESPOIRMALL@ESPOIR.COM